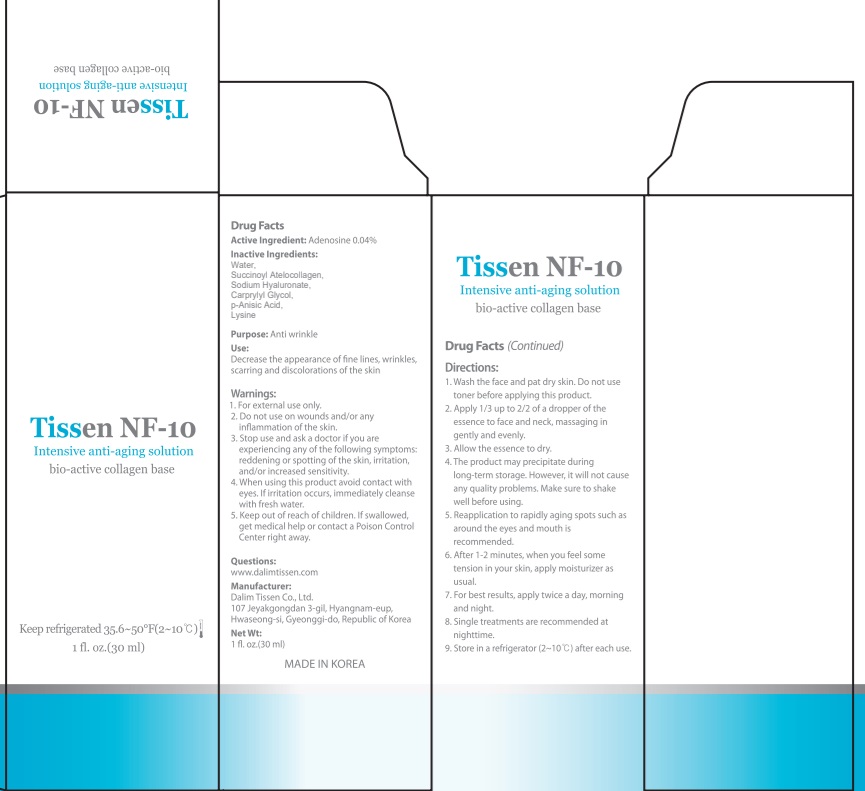 DRUG LABEL: Tissen NF 10
NDC: 42491-1100 | Form: LIQUID
Manufacturer: Dalim Tissen
Category: otc | Type: HUMAN OTC DRUG LABEL
Date: 20241125

ACTIVE INGREDIENTS: ADENOSINE 0.012 g/30 mL
INACTIVE INGREDIENTS: WATER; HYALURONATE SODIUM

ACTIVE INGREDIENT

Active ingredients: Adenosine 0.04%

INACTIVE INGREDIENT

Inactive ingredients:

Water, Succinoyl atelocollagen, Sodium hyaluronate, Methyl paraben, Propyl paraben, Lysine, L-

PURPOSE

Purpose: Anti wrinkle

WARNINGS

1. For external use only.
2. Do not use on wounds and/or any inflammation of the skin.
3. Stop use and ask a doctor if you are experiencing any of the following symptoms: reddening or spotting of the skin, irritation, and/or increased sensitivity.
4. When using this product avoid contact with eyes. If irritation occurs, immediately cleanse with fresh water.
5. Keep out of reach of children. If swallowed, get medical help or contact a Poison Control Center right away.

KEEP OUT OF REACH OF CHILDREN

Uses

Uses: Decrease the appearance of fine lines, wrinkles, scarring and discolorations of the skin

Directions

1. Wash the face and pat dry skin. Do not use toner before applying this product.
2. Apply 1/3 up to 2/2 of a dropper of the essence to face and neck, massaging in gently and evenly.
3. Allow the essence to dry.
4. The product may precipitate during long-term storage. However, it will not cause any quality problems. Make sure to shake well before using.
5. Reapplication to rapidly aging spots such as around the eyes and mouth is recommended.
6. After 1-2 minutes, when you feel some tension in your skin, apply moisturizer as usual.
7. For best results, apply twice a day, morning and night.
8. Single treatments are recommended at nighttime.
9. Store in a refrigerator (2-15℃) after each use.